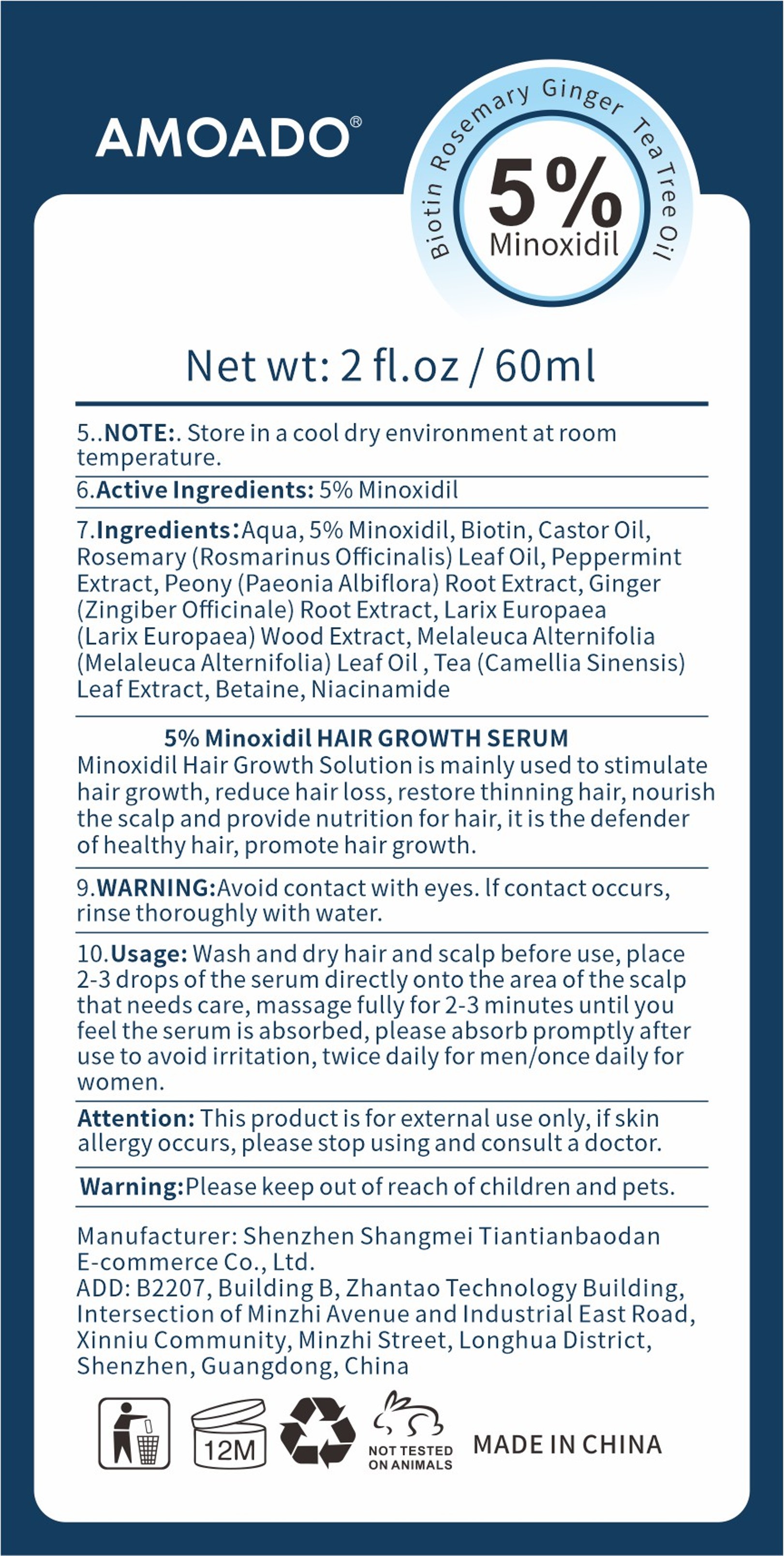 DRUG LABEL: 5% Minoxidil Hair Growth Serum
NDC: 85158-001 | Form: LIQUID
Manufacturer: Shenzhen Shangmei Tiantianbaodan E-commerce Co., Ltd
Category: homeopathic | Type: HUMAN OTC DRUG LABEL
Date: 20250115

ACTIVE INGREDIENTS: MINOXIDIL 0.05 g/1 mL
INACTIVE INGREDIENTS: GINGER; LARIX DECIDUA WOOD; BETAINE; NIACINAMIDE; CASTOR OIL; ROSMARINUS OFFICINALIS (ROSEMARY) LEAF OIL; BIOTIN; TEA LEAF; PEPPERMINT; PAEONIA LACTIFLORA ROOT; AQUA; MELALEUCA ALTERNIFOLIA LEAF

5% Minoxidil Hair Growth Serum

ACTIVE INGREDIENT

Minoxidil 5%

PURPOSE

hair growth

KEEP OUT OF REACH OF CHILDREN

Please keep out of reach of children and pets

INDICATIONS AND USAGE

Minoxidil Hair Growth Solution is mainly used to stimulatehair growth,reduce hairloss, restore thinninghair, nourishthe scalp and provide nutrition for hair, itis the defenderof healthy hair, promote hair growth.

WARNINGS

WARNING:Avoid contact with eyes.lf contact occurs,rinse thoroughly with water.

DOSAGE AND ADMINISTRATION

Usage:Wash and dry hair and scalp before use,place2-3 drops ofthe serum directly onto the area of the scalpthat needs care, massage fully for 2-3 minutes until youfeelthe serum is absorbed,please absorb promptly afteruse to avoid irritation,twice daily for men/once daily forwomen.

STORAGE AND HANDLING

NOTE:.Store in a cool dryenvironment at room

INACTIVE INGREDIENT

AQUA
BIOTIN
CASTOR OIL
ROSEMARY (ROSMARINUS OFFICINALIS) LEAF OIL
PEPPERMINT EXTRACT
PEONY (PAEONIA ALBIFLORA) ROOT EXTRACT
GINGER (ZINGIBER OFFICINALE) ROOT EXTRACT
LARIX EUROPAEA (LARIX EUROPAEA) WOOD EXTRACT
MELALEUCA ALTERNIFOLIA (MELALEUCA ALTERNIFOLIA) LEAF OIL
TEA (CAMELLIA SINENSIS) LEAF EXTRACT
BETAINE
NIACINAMIDE